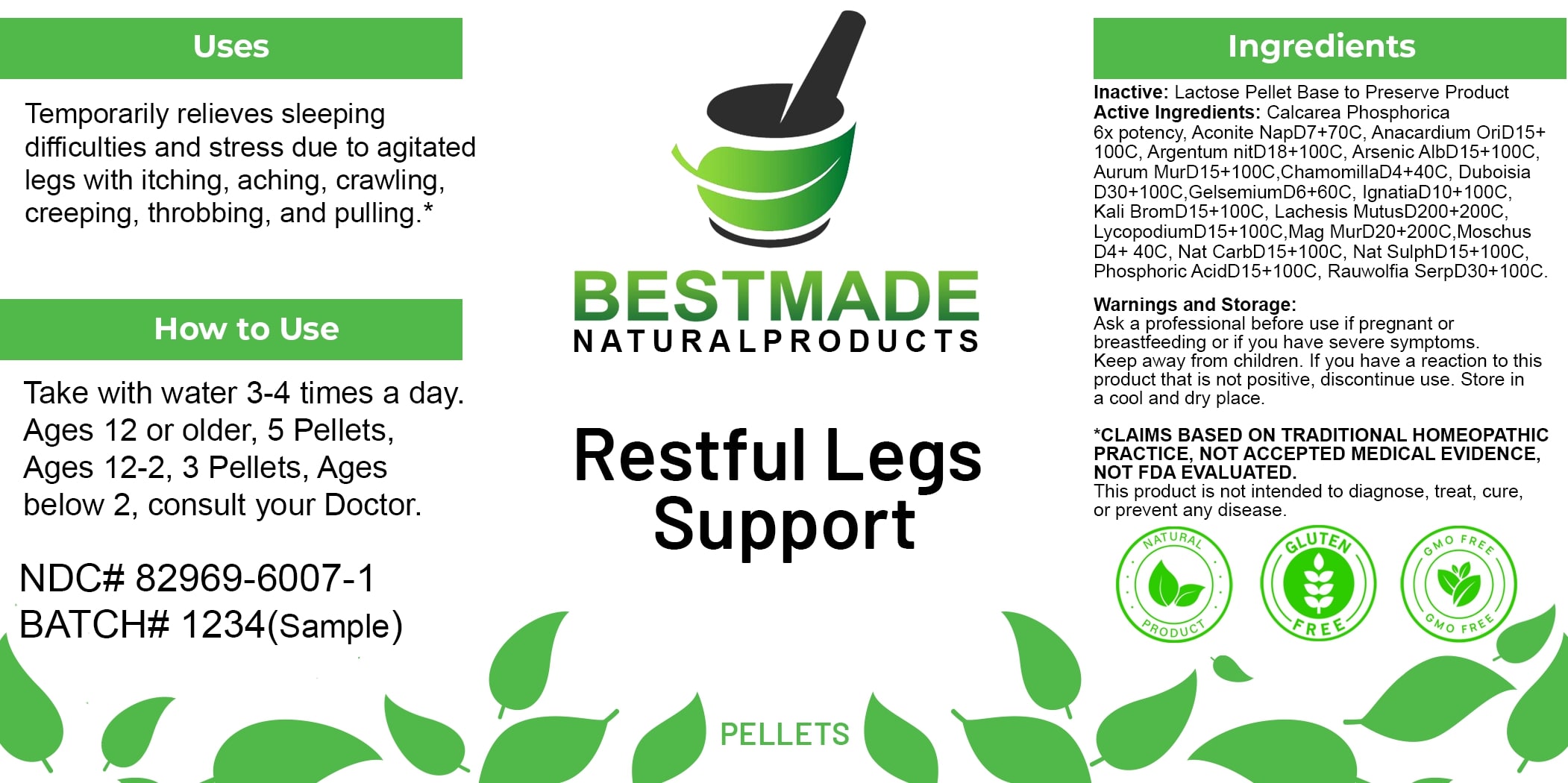 DRUG LABEL: Bestmade Natural Products Restful Legs Support
NDC: 82969-6007 | Form: TABLET, SOLUBLE
Manufacturer: Bestmade Natural Products
Category: homeopathic | Type: HUMAN OTC DRUG LABEL
Date: 20250314

ACTIVE INGREDIENTS: MOSCHUS MOSCHIFERUS MUSK SAC RESIN 100 [hp_C]/100 [hp_C]; PHOSPHORIC ACID 100 [hp_C]/100 [hp_C]; POTASSIUM BROMIDE 100 [hp_C]/100 [hp_C]; STRYCHNOS IGNATII SEED 100 [hp_C]/100 [hp_C]; SODIUM CARBONATE 100 [hp_C]/100 [hp_C]; GOLD TRICHLORIDE 100 [hp_C]/100 [hp_C]; MATRICARIA CHAMOMILLA 100 [hp_C]/100 [hp_C]; DUBOISIA MYOPOROIDES LEAF 100 [hp_C]/100 [hp_C]; LYCOPODIUM CLAVATUM SPORE 100 [hp_C]/100 [hp_C]; MAGNESIUM CHLORIDE 100 [hp_C]/100 [hp_C]; ACONITUM NAPELLUS 100 [hp_C]/100 [hp_C]; TRIBASIC CALCIUM PHOSPHATE 100 [hp_C]/100 [hp_C]; GELSEMIUM SEMPERVIRENS ROOT 100 [hp_C]/100 [hp_C]; SODIUM SULFATE 100 [hp_C]/100 [hp_C]; RAUWOLFIA SERPENTINA 100 [hp_C]/100 [hp_C]; LACHESIS MUTA VENOM 100 [hp_C]/100 [hp_C]; SEMECARPUS ANACARDIUM JUICE 100 [hp_C]/100 [hp_C]; ARSENIC TRIOXIDE 100 [hp_C]/100 [hp_C]; SILVER NITRATE 100 [hp_C]/100 [hp_C]
INACTIVE INGREDIENTS: LACTOSE 100 [hp_C]/100 [hp_C]

Restful Legs Support

DOSAGE AND ADMINISTRATION

How to Use

Take with water 3-4 times a day. Ages 12 or older, 5 Pellets, Ages 12-2, 3 Pellets, Ages below 2, consult your Doctor.

INACTIVE INGREDIENT

Ingredients

Inactive: Lactose Pellet Base to Preserve Remedy

ACTIVE INGREDIENT

Active Ingredients: Calcarea Phosphorica 6x potency, Aconite NapD7+70C, Anacardium OriD15+ 100C, Argentum nitD18+100C, Arsenic AlbD15+100C, Aurum MurD15+100C, ChamomillaD4+40C, Duboisia D30+100C, GelsemiumD6+60C, IgnatiaD10+100C, Kali BromD15+100C, Lachesis MutusD200+200C, LycopodiumD15+100C, Mag MurD20+200C, Moschus D4+40C, Nat CarbD15+100C, Nat SulphD15+100C, Phosphoric AcidD15+100C, Rauwolfia SerpD30+100C.

Uses

Temporarily relieves sleeping difficulties and stress due to agitated legs with itching, aching, crawling creeping, throbbing, and pulling.*

*CLAIMS BASED ON TRADITIONAL HOMEOPATHIC PRACTICE, NOT ACCEPTED MEDICAL EVIDENCE, NOT FDA EVALUATED.

This product is not intended to diagnose, treat, cure, or prevent any disease.

Uses

Temporarily relieves sleeping difficulties and stress due to agitated legs with itching, aching, crawling creeping, throbbing, and pulling.*

*CLAIMS BASED ON TRADITIONAL HOMEOPATHIC PRACTICE, NOT ACCEPTED MEDICAL EVIDENCE, NOT FDA EVALUATED.

This product is not intended to diagnose, treat, cure, or prevent any disease.

KEEP OUT OF REACH OF CHILDREN

Warnings and Storage:

Ask a professional before use if pregnant or breastfeeding or if you have severe symptoms. Keep away from children. If you have a reaction to this product that is not positive, discontinue use. Store in a cool and dry place.

Warnings and Storage:

Ask a professional before use if pregnant or breastfeeding or if you have severe symptoms. Keep away from children. If you have a reaction to this product that is not positive, discontinue use. Store in a cool and dry place.

*CLAIMS BASED ON TRADITIONAL HOMEOPATHIC PRACTICE, NOT ACCEPTED MEDICAL EVIDENCE NOT FDA EVALUATED.

This product is not intended to diagnose, treat, cure, or prevent any disease.

Entire package label